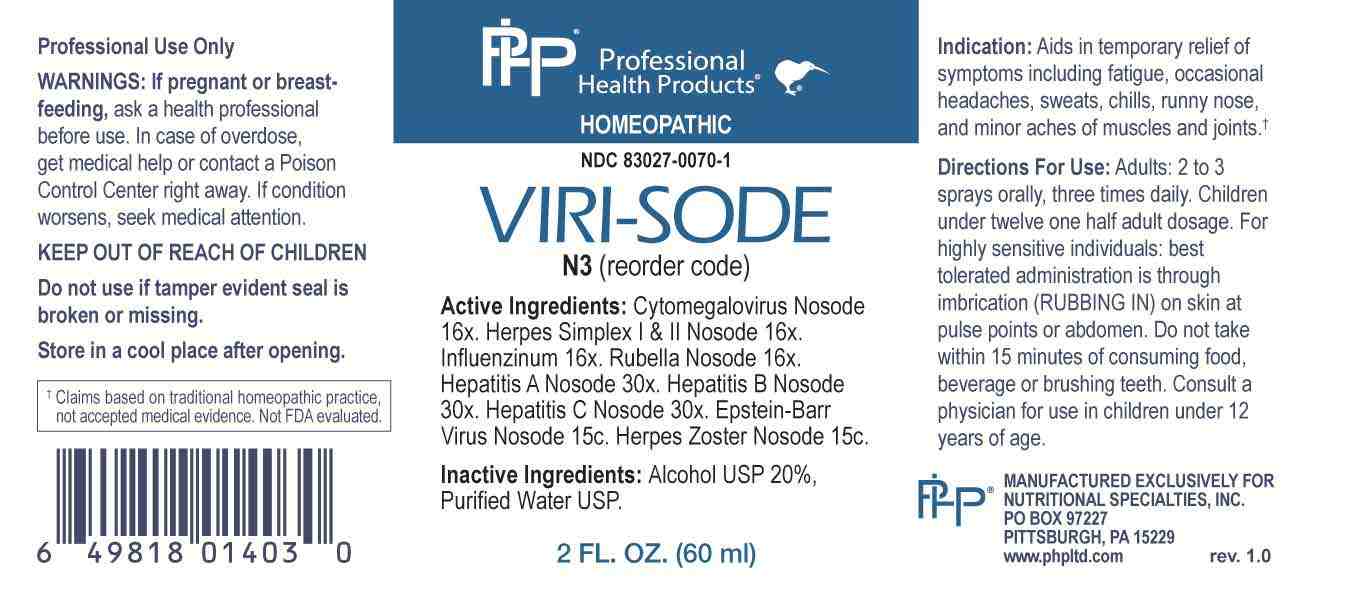 DRUG LABEL: Viri Sode
NDC: 83027-0070 | Form: SPRAY
Manufacturer: Nutritional Specialties, Inc.
Category: homeopathic | Type: HUMAN OTC DRUG LABEL
Date: 20250515

ACTIVE INGREDIENTS: HUMAN HERPESVIRUS 5 16 [hp_X]/1 mL; HUMAN HERPESVIRUS 1 16 [hp_X]/1 mL; HUMAN HERPESVIRUS 2 16 [hp_X]/1 mL; INFLUENZA A VIRUS A/VICTORIA/2570/2019 IVR-215 (H1N1) ANTIGEN (UV, FORMALDEHYDE INACTIVATED) 16 [hp_X]/1 mL; INFLUENZA A VIRUS A/DARWIN/9/2021 IVR-228 (H3N2) ANTIGEN (UV, FORMALDEHYDE INACTIVATED) 16 [hp_X]/1 mL; INFLUENZA B VIRUS B/AUSTRIA/1359417/2021 BVR-26 ANTIGEN (UV, FORMALDEHYDE INACTIVATED) 16 [hp_X]/1 mL; INFLUENZA B VIRUS B/PHUKET/3073/2013 ANTIGEN (UV, FORMALDEHYDE INACTIVATED) 16 [hp_X]/1 mL; RUBELLA VIRUS 16 [hp_X]/1 mL; HEPATITIS A VIRUS 30 [hp_X]/1 mL; HEPATITIS B VIRUS 30 [hp_X]/1 mL; HEPATITIS C VIRUS 30 [hp_X]/1 mL; HUMAN HERPESVIRUS 4 15 [hp_C]/1 mL; HUMAN HERPESVIRUS 3 15 [hp_C]/1 mL
INACTIVE INGREDIENTS: WATER; ALCOHOL

DRUG FACTS:

ACTIVE INGREDIENTS:

Cytomegalovirus Nosode 16X, Herpes Simplex I Nosode 16X, Herpes Simplex II Nosode 16, Influenzinum 16X, Rubella Nosode 16X, Hepatitis A Nosode 30X, Hepatitis B Nosode 30X, Hepatitis C Nosode 30X, Epstein Barr Virus Nosode 15C, Herpes Zoster Nosode 15C.

PURPOSE:

Aids in temporary relief of symptoms including fatigue, occasional headaches, sweats, chills, runny nose, and minor aches of muscles and joints.†

†Claims based on traditional homeopathic practice, not accepted medical evidence. Not FDA evaluated.

WARNINGS:

Professional Use Only

If pregnant or breast-feeding, ask a health professional before use.

In case of overdose, get medical help or contact a Poison Control Center right away.

If condition worsens, seek medical attention.

KEEP OUT OF REACH OF CHILDREN

Do not use if tamper evident seal is broken or missing.

Store in a cool place after opening

KEEP OUT OF REACH OF CHILDREN:

In case of overdose, get medical help or contact a Poison Control Center right away.

DIRECTIONS:

Adults: 2 to 3 sprays orally, three times daily. Children under twelve one half adult dosage.

For high sensitive individuals: best tolerated administration is through imbrication (RUBBING IN) on skin at pulse points or abdomen.

Do not take within 15 minutes of consuming food, beverage or brushing teeth. Consult a physician for use in children under 12 years of age.

INDICATIONS:

Aids in temporary relief of symptoms including fatigue, occasional headaches, sweats, chills, runny nose, and minor aches of muscles and joints.†

†Claims based on traditional homeopathic practice, not accepted medical evidence. Not FDA evaluated.

INACTIVE INGREDIENTS:

Alcohol USP 20%, Purified Water USP.

QUESTIONS:

MANUFACTURED EXCLUSIVELY FOR

NUTRITIONAL SPECIALTIES, INC.

PO BOX 97227

PITTSBURG, PA 15229

www.phpltd.com

PACKAGE LABEL DISPLAY:

Professional

Health Products

HOMEOPATHIC

NDC 83027-0070-1

VIRI-SODE

2 FL. OZ (60 ml)